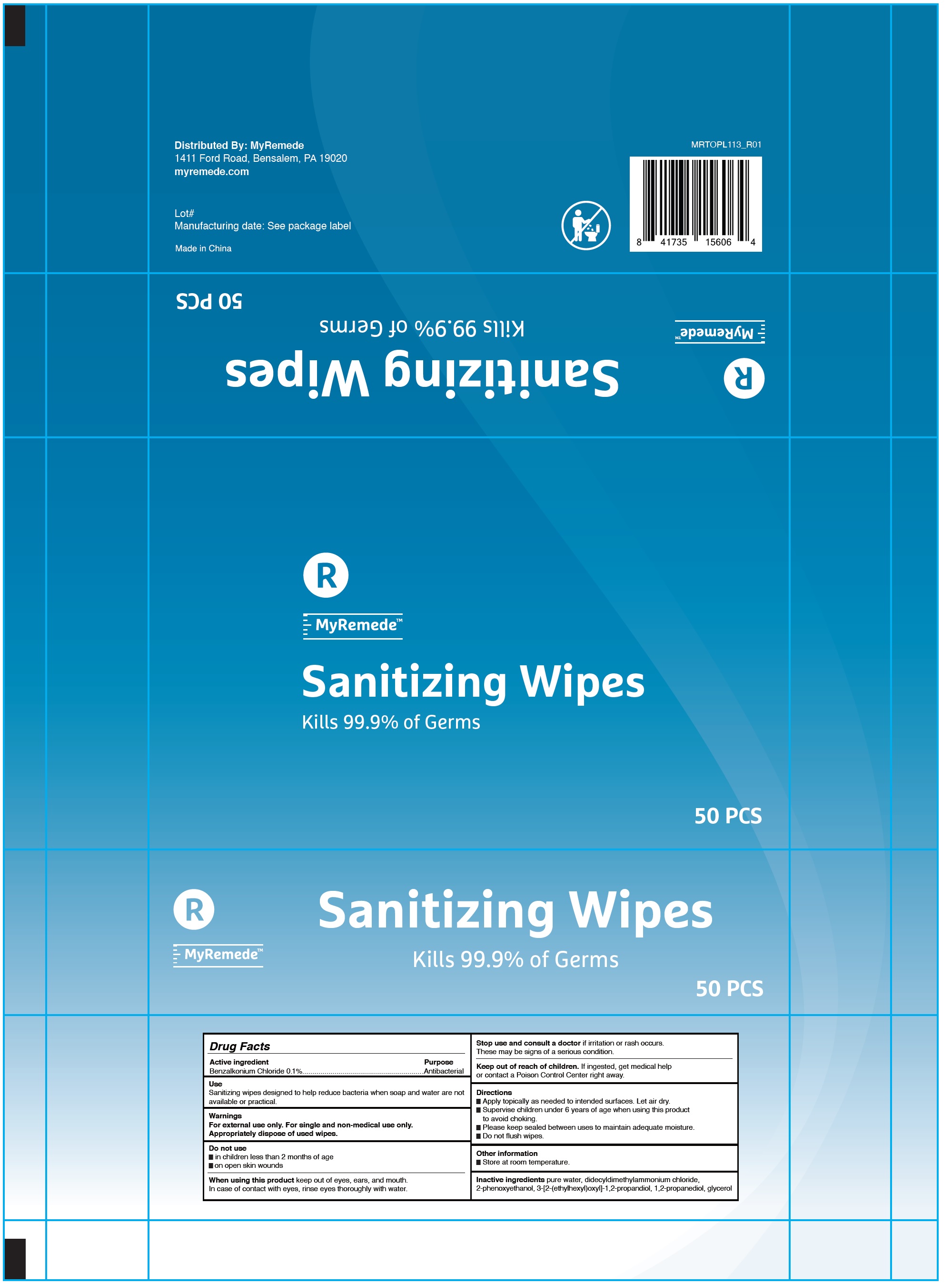 DRUG LABEL: MyRemede Sanitizing Wipes
NDC: 77529-001 | Form: CLOTH
Manufacturer: Remede Organics, Inc
Category: otc | Type: HUMAN OTC DRUG LABEL
Date: 20200803

ACTIVE INGREDIENTS: BENZALKONIUM CHLORIDE 1 mg/1 mL
INACTIVE INGREDIENTS: WATER; DIDECYLDIMONIUM CHLORIDE; PHENOXYETHANOL; PROPYLENE GLYCOL; GLYCERIN

MyRemede Sanitizing Wipes

Active Ingredient

Benzalkonium Chloride 0.1%

Purpose

Antibacterial

Use

Sanitizing wipes designed to help reduce bacteria when soap and water are not available or practical.

Warnings

For external use only. For single and non-medical use only. Appropriately dispose of used wipes.

Do not use

- in children less than 2 months of age
- on open skin wounds

When using this product

keep out of eyes, ears, and mouth. In case of contact with eyes, rinse eyes thoroughly with water.

Stop use and consult a doctor if

irritation or rash occurs. These may be signs of a serious condition.

Keep out of reach of children.

If ingested, get medical help or contact a Poison Control Center right away.

Directions

- Apply topicall as needed to intended surfaces. Let air dry.
- Supervise children under 6 years of age when using this product to avoid choking.
- Please keep sealed between uses to maintain adequate moisture.
- Do not flush wipes.

Other Information

Store at room temperature.

Inactive Ingredients

Pure water, Didecyldimethylammonium chloride, 2-Phenoxyethanol, 3-[2-(Ethylhexyloxy]-1,2-propanediol, 1,2-Propanediol, Glycerol